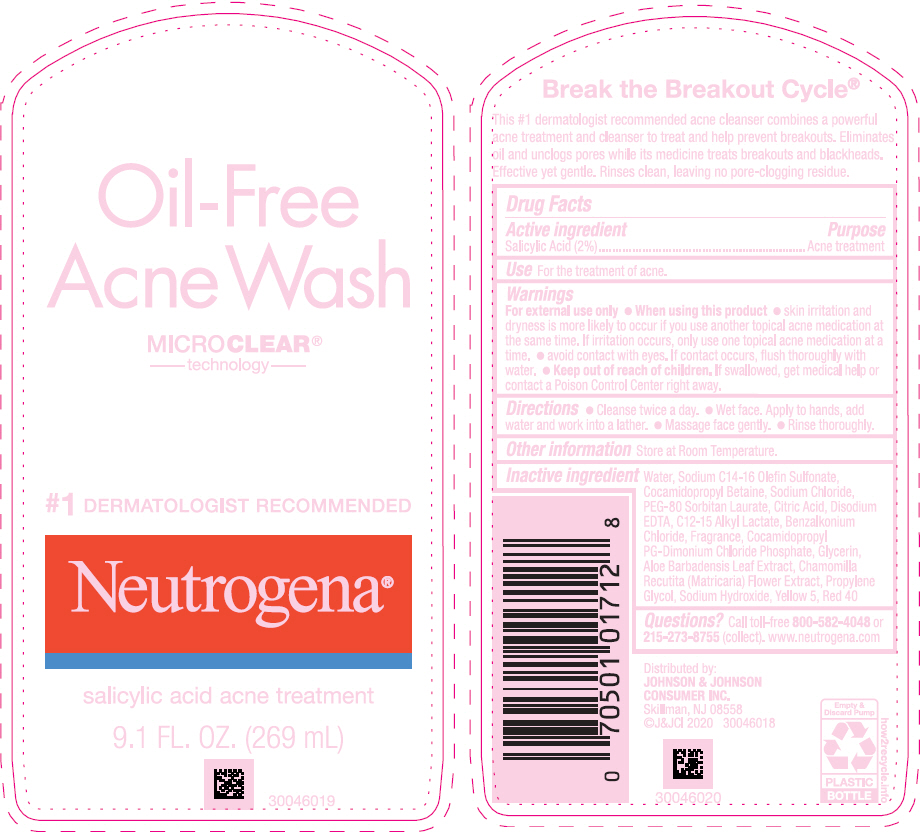 DRUG LABEL: Neutrogena Oil Free Acne Wash
NDC: 69968-0675 | Form: LIQUID
Manufacturer: Kenvue Brands LLC
Category: otc | Type: HUMAN OTC DRUG LABEL
Date: 20260112

ACTIVE INGREDIENTS: SALICYLIC ACID 20 mg/1 mL
INACTIVE INGREDIENTS: WATER; SODIUM C14-16 OLEFIN SULFONATE; COCAMIDOPROPYL BETAINE; SODIUM CHLORIDE; PEG-80 SORBITAN LAURATE; CITRIC ACID MONOHYDRATE; EDETATE DISODIUM; C12-15 ALKYL LACTATE; BENZALKONIUM CHLORIDE; COCAMIDOPROPYL PROPYLENE GLYCOL-DIMONIUM CHLORIDE PHOSPHATE; GLYCERIN; ALOE VERA LEAF; CHAMOMILE; PROPYLENE GLYCOL; SODIUM HYDROXIDE; FD&C YELLOW NO. 5; FD&C RED NO. 40

Neutrogena® Oil-Free Acne Wash

Drug Facts

Active ingredient

Salicylic Acid (2%)

Purpose

Acne treatment

Use

For the treatment of acne.

Warnings

For external use only.

- When using this product
  - skin irritation and dryness is more likely to occur if you use another topical acne medication at the same time. If irritation occurs, only use one topical acne medication at a time.
  - avoid contact with eyes. If contact occurs, flush thoroughly with water.

- Keep out of reach of children. If swallowed, get medical help or contact a Poison Control Center right away.

Directions

- Cleanse twice a day.
- Wet face. Apply to hands, add water and work into a lather.
- Massage face gently.
- Rinse thoroughly.

Other information

Store at Room Temperature.

Inactive ingredients

Water, Sodium C14-16 Olefin Sulfonate, Cocamidopropyl Betaine, Sodium Chloride, PEG-80 Sorbitan Laurate, Citric Acid, Disodium EDTA, C12-15 Alkyl Lactate, Benzalkonium Chloride, Fragrance, Cocamidopropyl PG-Dimonium Chloride Phosphate, Glycerin, Aloe Barbadensis Leaf Extract, Chamomilla Recutita (Matricaria) Flower Extract, Propylene Glycol, Sodium Hydroxide, Yellow 5, Red 40

Questions?

Call toll-free 800-582-4048 or 215-273-8755 (collect). www.neutrogena.com

Distributed by:
JOHNSON & JOHNSON
CONSUMER INC.
Skillman, NJ 08558

PRINCIPAL DISPLAY PANEL - 269 mL Bottle Label

Oil-Free
Acne Wash
MICRO CLEAR®
technology

#1 DERMATOLOGIST RECOMMENDED
Neutrogena®
salicylic acid acne treatment

9.1 FL. OZ. (269 mL)